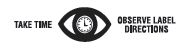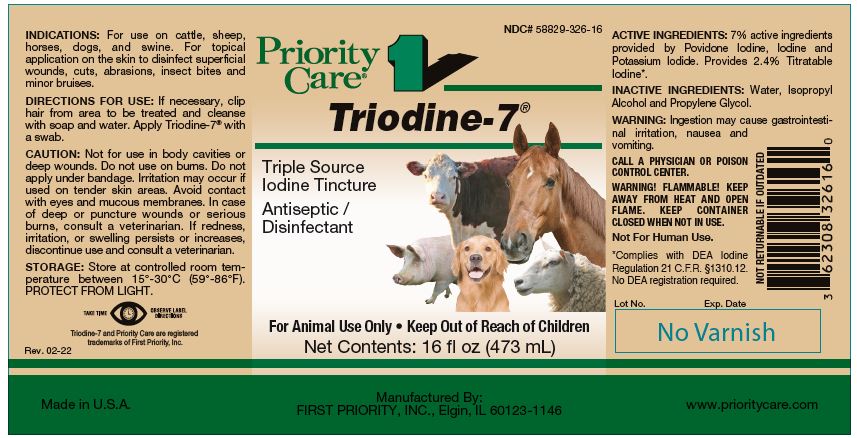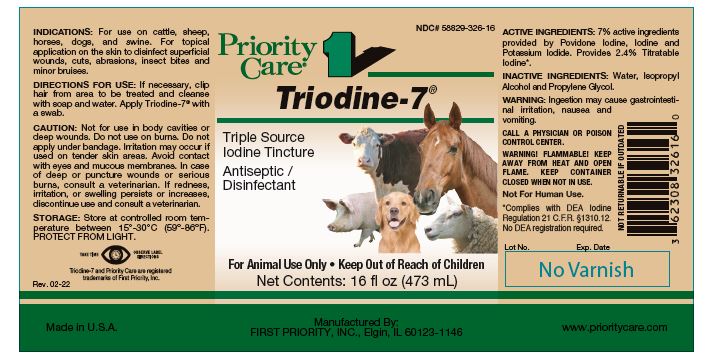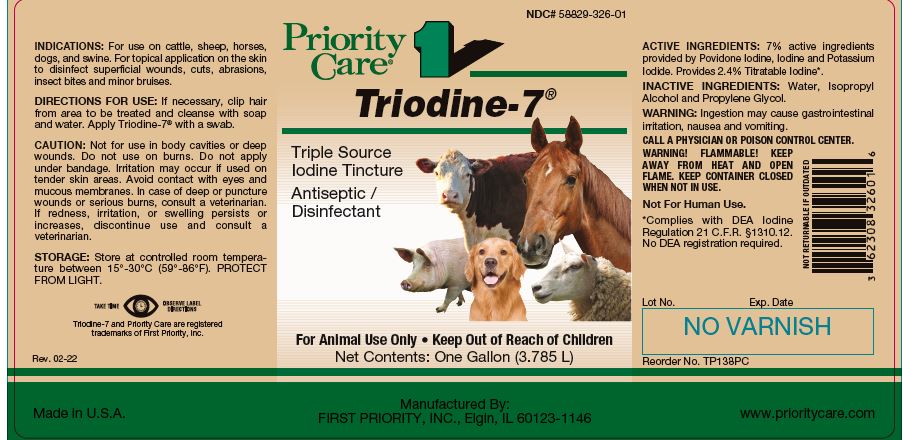 DRUG LABEL: Triodine
NDC: 58829-326 | Form: SOLUTION
Manufacturer: FIRST PRIORITY INCORPORATED
Category: animal | Type: OTC ANIMAL DRUG LABEL
Date: 20260223

ACTIVE INGREDIENTS: IODINE 2.1 mg/1 mL; POVIDONE-IODINE 3.0 mg/1 mL; POTASSIUM IODIDE 2.0 mg/1 mL

Triodine-7®

PURPOSE

Triple Source Iodine Tincture Antiseptic / Disinfectant

KEEP OUT OF REACH OF CHILDREN

For Animal Use Only • Keep Out of Reach of Children

INDICATIONS:

For use on cattle, sheep, horses, dogs, and swine. For topical application on the skin to disinfect superficial wounds, cuts, abrasions, insect bites and minor bruises.

DIRECTIONS FOR USE:

If necessary, clip hair from area to be treated and cleanse with soap and water. Apply Triodine-7® with a swab.

CAUTION:

Not for use in body cavities or deep wounds. Do not use on burns. Do not apply under bandage. Irritation may occur if used on tender skin areas. Avoid contact with eyes and mucous membranes. In case of deep or puncture wounds or serious burns, consult a veterinarian. If redness, irritation, or swelling persists or increases, discontinue use and consult a veterinarian.

STORAGE:

Store at controlled room temperature between 15°-30°C (59°-86°F). PROTECT FROM LIGHT.

Triodine-7 and Priority Care are registered trademarks of First Priority, Inc.

ACTIVE INGREDIENTS:

7% active ingredients provided by Povidone Iodine, Iodine and Potassium Iodide. Provides 2.4% Titratable Iodine*.

INACTIVE INGREDIENTS:

Water, Isopropyl Alcohol and Propylene Glycol.

WARNING:

Ingestion may cause gastrointestinal irritation, nausea and vomiting.

CALL A PHYSICIAN OR POISON CONTROL CENTER.

WARNING! FLAMMABLE! KEEP AWAY FROM HEAT AND OPEN FLAME. KEEP CONTAINER CLOSED WHEN NOT IN USE.

Not For Human Use.

Net Contents:

16 fl oz (473 mL) Reorder No. TP135PC

32 fl oz (960 mL) Reorder No. TP137PC

One Gallon (3.785 L) Reorder No. TP138PC

INFORMATION FOR OWNERS/CAREGIVERS

*Complies with DEA Iodine Regulation 21 C.F.R. §1310.12. No DEA registration required.

Made in U.S.A.

Manufactured By: FIRST PRIORITY, INC., Elgin, IL 60123-1146

www.prioritycare.com

NOT RETURNABLE IF OUTDATED